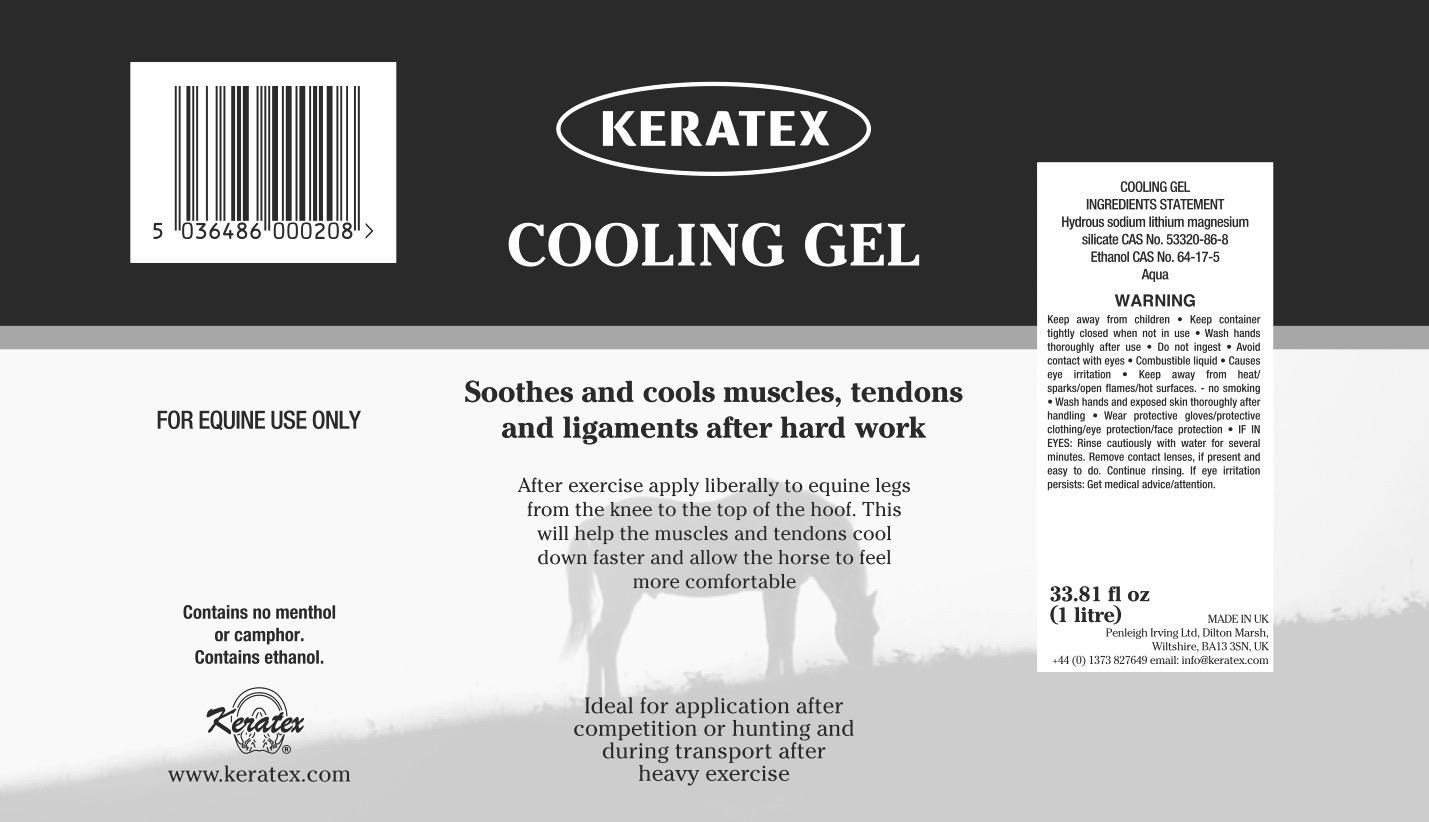 DRUG LABEL: Keratex
NDC: 27426-016 | Form: LIQUID
Manufacturer: Penleigh Irving Ltd
Category: animal | Type: OTC ANIMAL DRUG LABEL
Date: 20181221

ACTIVE INGREDIENTS: ALCOHOL 111.1 mL/1 L; Water 870.9 mL/1 L
INACTIVE INGREDIENTS: Laponite

SAFE HANDLING WARNING

Keep away from children. Keep container tightly closed when not in use. Wash hands thoroughly after use. Do not ingest. Avoid contact with eyes. Combustible liquid. Causes eye irritation. Keep away from heat/sparks/open flames/hot surfaces - no smoking. Wash hands and exposed skin thoroughly after handling. Wear protective gloves/protective clothing/eye protection/face protection. IF IN EYES: Rinse cautiously with water for several minutes. Remove contact lenses, if present and easy to do. Continue rinsing. If eye irritations persists: Get medical advice/attention.

PACKAGE LABEL

Keratex Cooling Gel

Soothes and cools muscles, tendons and ligaments after hard work

After exercise apply liberally to equine legs from the knee to the top of the hoof. This will help the muscles and tendons cool down faster and allow the horse to feel more comfortable.

Ideal for application after competition or hunting and during transport after heavy exercise.

For Equine Use Only. Contains no menthol or camphor. Contains ethanol.

Cooling Gel Ingredients Statement: Hydrous sodium lithium magnesium silicate CAS No. 53320-86-6. Ethanol CAS No. 64-17-5. Aqua.

Keep away from children. Keep container tightly closed when not in use. Wash hands thoroughly after use. Do not ingest. Avoid contact with eyes. If in eyes: Rinse cautiously with water for several minutes. Remove contact lenses if present and easy to do. Continue rinsing.

33.8 fl oz (1 Litre)

MADE IN UK

Penleigh Irving Ltd.

Dilton Marsh, Wiltshire, BK13 3SN, UK

+44 (0) 1373 827649 email: info@keratex.com

www.keratex.com